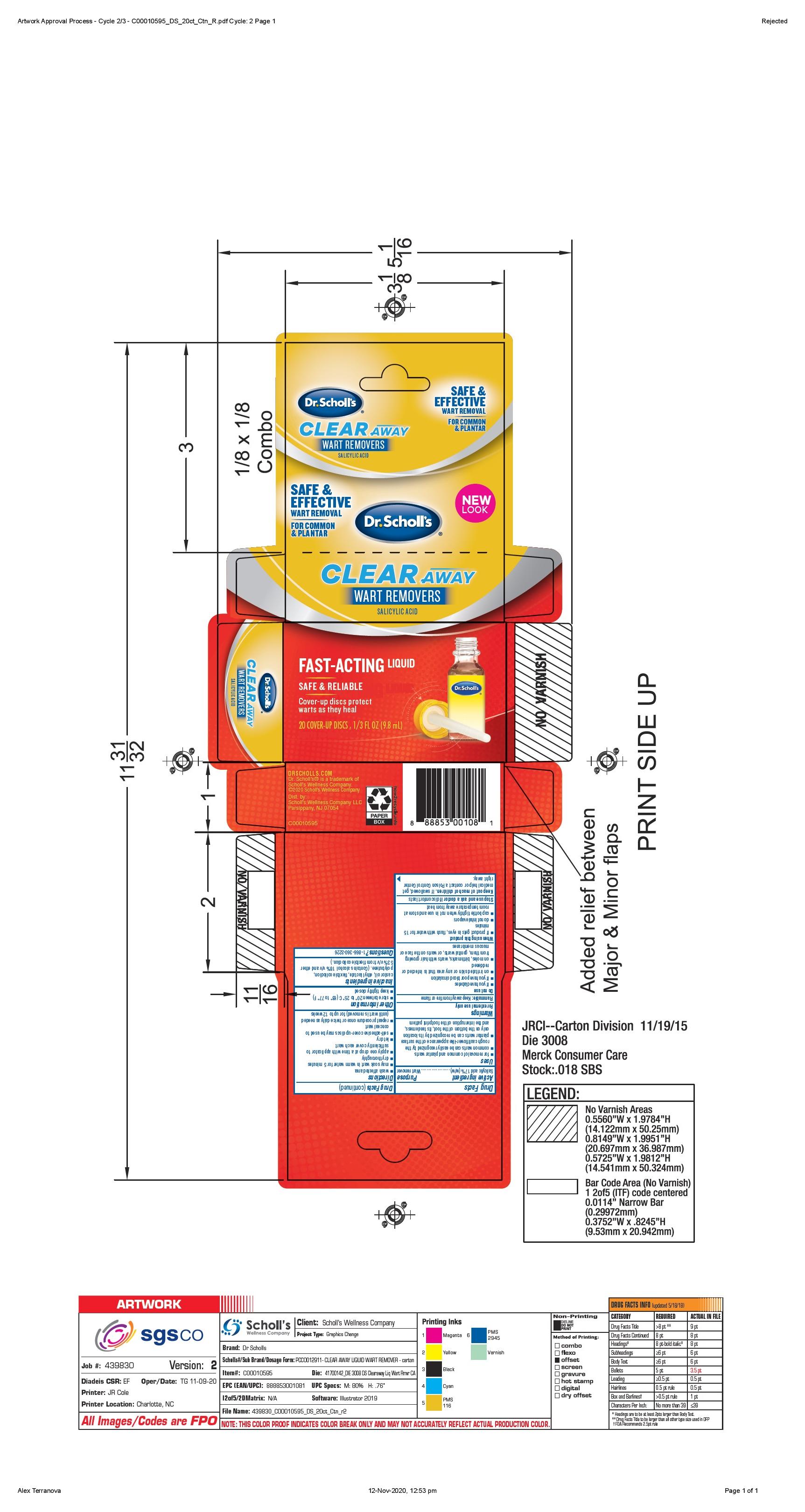 DRUG LABEL: Scholls Wellness Company LLC
NDC: 73469-0118 | Form: LIQUID
Manufacturer: Scholls Wellness Company LLC
Category: otc | Type: HUMAN OTC DRUG LABEL
Date: 20220124

ACTIVE INGREDIENTS: SALICYLIC ACID 0.17 g/1 g
INACTIVE INGREDIENTS: CASTOR OIL

Clear Away Wart Removers

Drug Facts

Active Ingredient Purpose

Salicylic Acid 17%(w/w).......................Wart remover

Purpose

Wart remover

Uses

for the removal of common plantar warts
common warts can be easily recognized by the rough cauliflower-like appearance of the surface

plantar warts can be recognized by its location only at the bottom of the foot, its tenderness, and the interuption of the footprint pattern

Warnings

For external use only

Flammable: keep away from fire or flame

Do not use

if you have diabetes
if you have poor blood circulation
on irritated skin or any area that is infected or reddened

on moles, birthmarks, warts with hair growing from them, genital warts, or warts on the face or mucous membranes

When using this product

If product gets in eyes, flush with water for 15 minutes

do not inhale vapors

cap bottle tightly when not in use and store at room temperature away from heat

Stop use and ask a doctor if discomfort lasts

Keep out of reach of children. If swallowed,

get medical help or contact a Poison Control Center right away.

Directions

wash affected area

may soak wart in warm water for 5 minutes

dry thoroughly

apply one drop at a time with applicator to sufficiently cover each wart

let dry

self-adhesive cover-up disc may be used to cover wart

repeat procedure once or twice daily as needed (until wart is removed) for up to 12 weeks

Other information

store between 20ºC to 25ºC (68º to 77ºF).
keep tightly closed

Inactive ingredients

castor oil, ethyl lactate, flexible collodion polybutene. (contains alcohol 18% v/v and ether 53% v/v from flexible collodion).

Questions? 1-866-360-3226